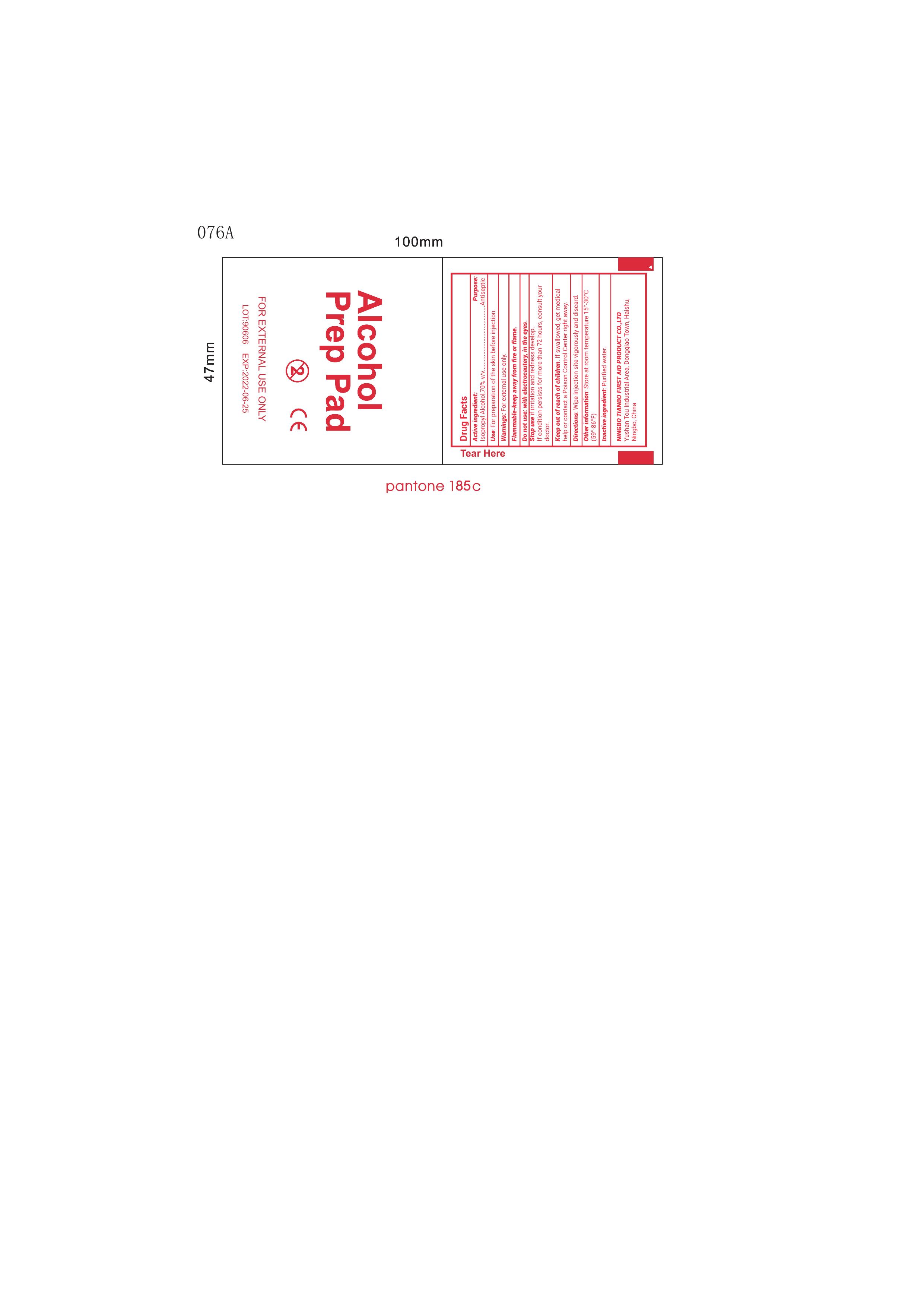 DRUG LABEL: Alcohol Prep Pads
NDC: 73288-001 | Form: SOLUTION
Manufacturer: NINGBO TIANBO FIRST AID PRODUCT CO., LTD.
Category: otc | Type: HUMAN OTC DRUG LABEL
Date: 20260112

ACTIVE INGREDIENTS: ISOPROPYL ALCOHOL 70 mL/100 mL
INACTIVE INGREDIENTS: WATER

73288-001

Active Ingredient: Isopropyl Alcohol 70%

Purpose: Antiseptic

INDICATIONS AND USAGE

Uses: For preparation of the skin before injection

Warnings:

For external use only

Flammable. Keek away from fire or flame.

Do not use with electrocautery in the eyes

Stop use if irritation and redness develop. If condition persists for more then 72 hours, consult your doctor.

Keep out of reach of children. If swallowed, get medical help or contact a Poison Control Center right away

DOSAGE AND ADMINISTRATION

Directions: Wipe injection site vigorously and discard

Other information

- Store at room temperature 15-30C (59-86F)

Inactive Ingredient

Purified Water